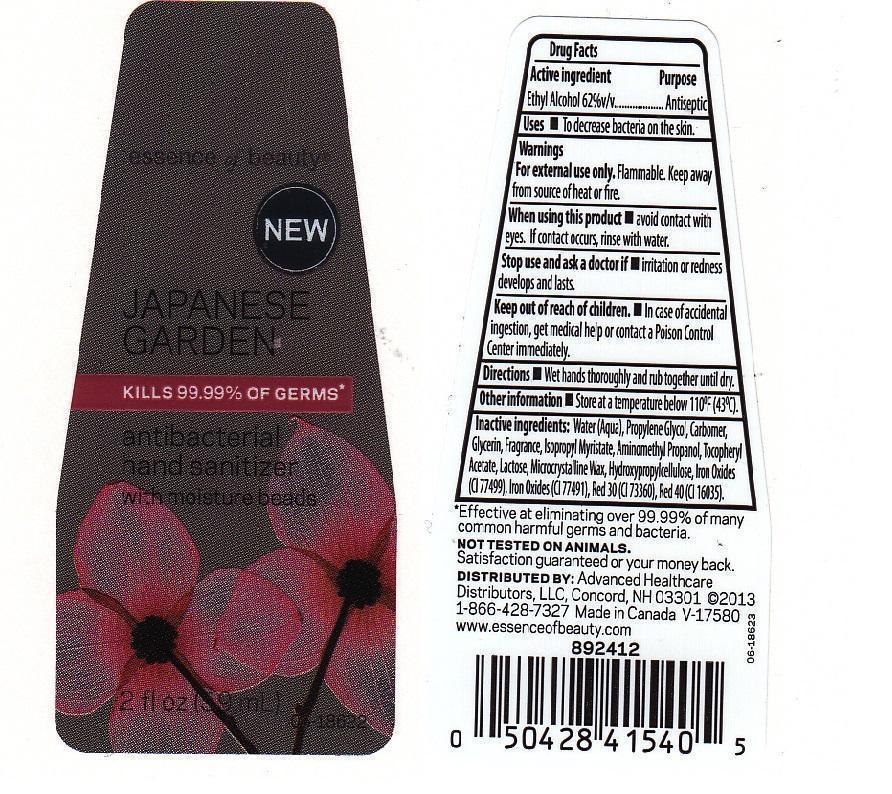 DRUG LABEL: ESSENCE OF BEAUTY
NDC: 59779-493 | Form: LIQUID
Manufacturer: CVS PHARMACY
Category: otc | Type: HUMAN OTC DRUG LABEL
Date: 20130709

ACTIVE INGREDIENTS: ALCOHOL 620 mg/1 mL
INACTIVE INGREDIENTS: WATER; PROPYLENE GLYCOL; CARBOMER 934; GLYCERIN; ISOPROPYL MYRISTATE; AMINOMETHYLPROPANOL; .ALPHA.-TOCOPHEROL ACETATE; LACTOSE; MICROCRYSTALLINE WAX; HYDROXYPROPYL CELLULOSE; FERROSOFERRIC OXIDE; FERRIC OXIDE RED; D&C RED NO. 30; FD&C RED NO. 40

DRUG FACTS

ACTIVE INGREDIENT

ETHYL ALCOHOL 62% V/V

PURPOSE

ANTISEPTIC

USES

TO DECREASE BACTERIA ON THE SKIN.

WARNINGS

FOR EXTERNAL USE ONLY. FLAMMABLE. KEEP AWAY FROM SOURCE OF HEAT OR FIRE.

WHEN USING THIS PRODUCT

AVOID CONTACT WITH EYES. IF CONTACT OCCURS, RINSE WITH WATER.

STOP USE AND ASK A DOCTOR IF

IRRITATION OR REDNESS DEVELOPS AND LASTS.

KEEP OUT OF REACH OF CHILDREN

IN CASE OF ACCIDENTAL INGESTION, GET MEDICAL HELP OR CONTACT A POISON CONTROL CENTER IMMEDIATELY.

DIRECTIONS

WET HANDS THOROUGHLY AND RUB TOGETHER UNTIL DRY.

OTHER INFORMATION

STORE AT A TEMPERATURE BELOW 110F (43C).

INACTIVE INGREDIENTS:

WATER (AQUA), PROPYLENE GLYCOL, CARBOMER, GLYCERIN, FRAGRANCE, ISOPROPYL MYRISTATE, AMINOMETHYL PROPANOL, TOCOPHERYL ACETATE, LACTOSE, MICROCRYSTALLINE WAX, HYDROXYPROPYLCELLULOSE, IRON OXIDES (CI 77499), IRON OXIDES (CI 77491), RED 30 (CI 73360), RED 40 (CI 16035).